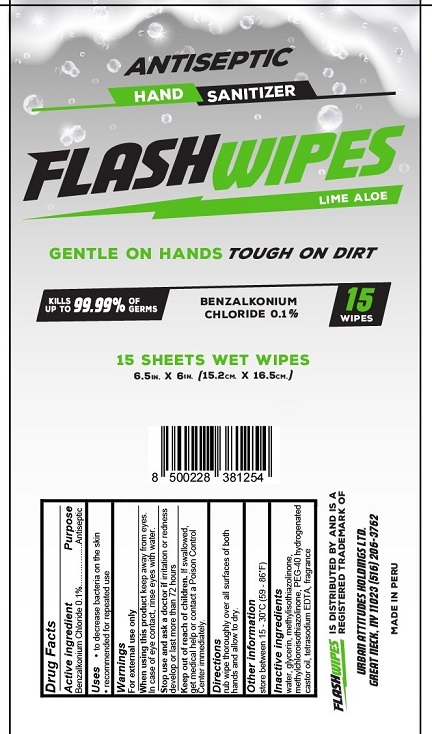 DRUG LABEL: FlashWipes
NDC: 77185-011 | Form: CLOTH
Manufacturer: Urban Attitudes Holdings Ltd
Category: otc | Type: HUMAN OTC DRUG LABEL
Date: 20200917

ACTIVE INGREDIENTS: BENZALKONIUM CHLORIDE 0.1 g/100 mL
INACTIVE INGREDIENTS: EDETATE SODIUM; METHYLISOTHIAZOLINONE; METHYLCHLOROISOTHIAZOLINONE; POLYOXYL 40 HYDROGENATED CASTOR OIL; WATER; GLYCERIN

Flash Wipes Lime Aloe

Drug Facts

Active ingredient

Benzalkonium Chloride 0.1%

Purpose
Antiseptic

Uses

- to decrease bacteria on the skin
- recommended for repeated use

Warnings

For external use only

When using this product keep away from eyes. In case of eye contact, rinse eyes with water.

Stop use and ask a doctor if irritation or redness develop or last more than 72 hours.

Keep out of reach of children. If swallowed, get medical help or contact a Poison Control Center immediately.

Directions

rub wipe thoroughly over all sufaces of both hands and allow to dry.

Other information

store between 15-30°C (59-86°F)

Inactive ingredients

water, glycerin, methylchloroisothiazolinone, methylisothiazonlinone, PEG-40 hydrogenated castor oil, tetrasodium EDTA, fragrance

MADE IN PERU

FLASH WIPES IS DISTRIBUTED BY AND IS A REGISTERED TRADEMARK OF

URBAN ATTITUDES HOLDINGS LTD.

GREAT NECK, NY 11023 (516) 206-3672

PACKAGE LABEL

ANTISEPTIC HAND SANITIZER
FLASHWIPES
LIME ALOE
GENTLE ON HANDS TOUGH ON DIRT
KILLS UP TO 99.99% OF GERMS
BENZALKONIUM CHLORIDE 0.1%
15 SHEETS WET WIPES
6.5 IN. x 6 IN. (15.2 CM x 16.5 CM)